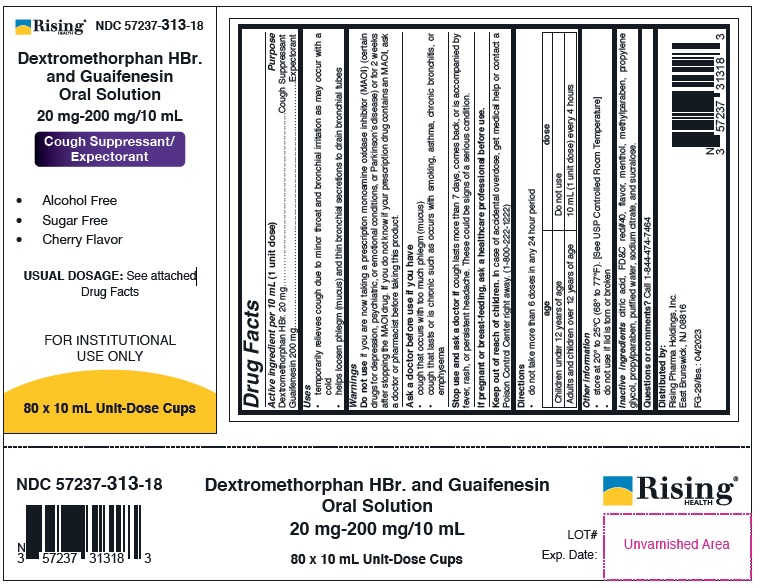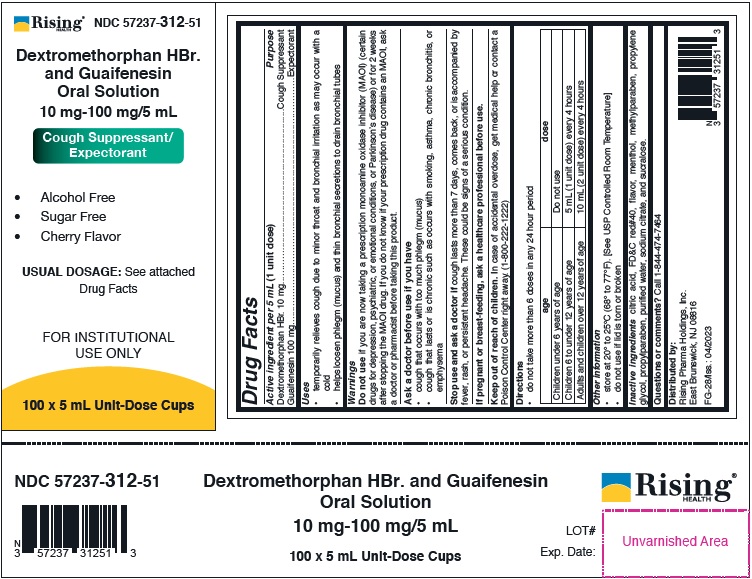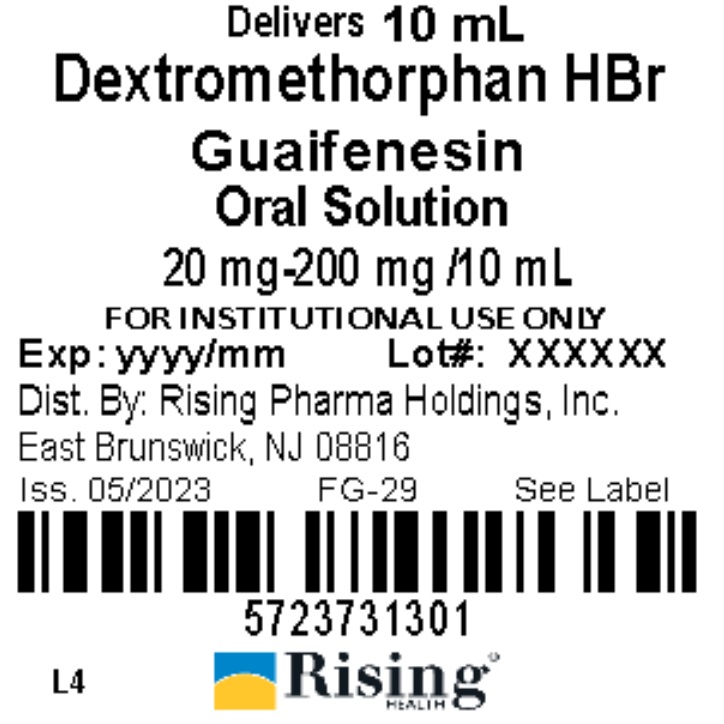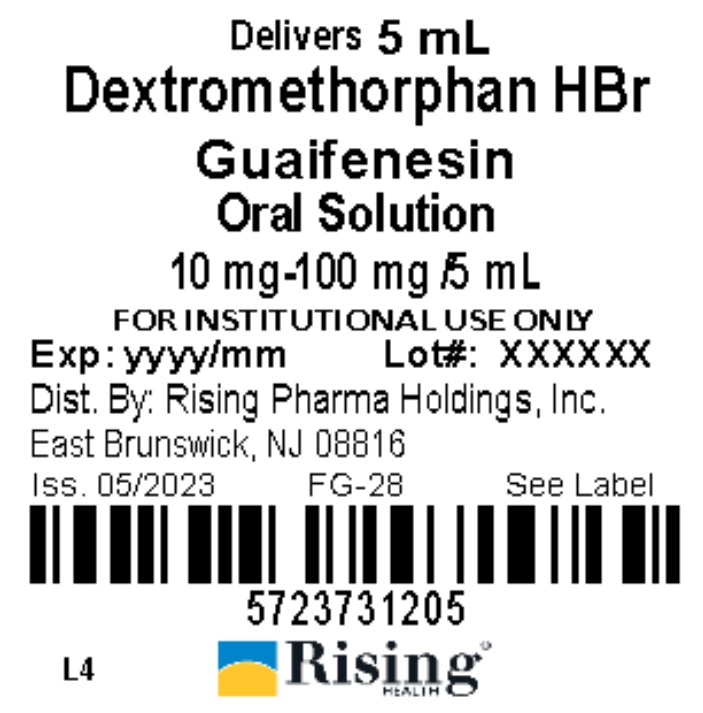 DRUG LABEL: Dextromethorphan HBr. and Guaifenesin
NDC: 57237-312 | Form: SOLUTION
Manufacturer: Rising Pharma Holdings, Inc.
Category: otc | Type: HUMAN OTC DRUG LABEL
Date: 20250701

ACTIVE INGREDIENTS: DEXTROMETHORPHAN HYDROBROMIDE 10 mg/5 mL; GUAIFENESIN 100 mg/5 mL
INACTIVE INGREDIENTS: ANHYDROUS CITRIC ACID; FD&C RED NO. 4; MENTHOL; METHYLPARABEN; PROPYLENE GLYCOL; PROPYLPARABEN; WATER; SODIUM CITRATE; SUCRALOSE

DRUG FACTS

10 mg-100 mg/5 mL -

Active ingredient per 5 mL (1 unit dose)

Dextromethorphan HBr. 10 mg

Guaifenesin 100 mg

20 mg-200 mg/10 mL -

Active ingredient per 10 mL (1 unit dose)

Dextromethorphan HBr. 20 mg

Guaifenesin 200 mg

Purpose

Cough Suppressant

Expectorant

Uses

• temporarily relieves cough due to minor throat and bronchial irritation as may occur with a cold
• helps loosen phlegm (mucus) and thin bronchial secretions to drain bronchial tubes

Warnings

Do not use if you are now taking a prescription monoamine oxidase inhibitor (MAOI) (certain drugs for depression, psychiatric, or emotional conditions, or Parkinson’s disease) or for 2 weeks after stopping the MAOI drug. If you do not know if your prescription drug contains an MAOI, ask a doctor or pharmacist before taking this product.

Ask a doctor before use if you have

• cough that occurs with too much phlegm (mucus)
• cough that lasts or is chronic such as occurs with smoking, asthma, chronic bronchitis, or emphysema

Stop use and ask a doctor if cough lasts more than 7 days, comes back, or is accompanied by fever, rash, or persistant headache. These could be signs of a serious condition.

PREGNANCY OR BREAST FEEDING

If pregnant or breast-feeding, ask a healthcare professional before use.

Keep out of reach of children. In case of accidental overdose, get medical help or contact a Poison Control Center right away. (1-800-222-1222)

Directions

• do not take more than 6 doses in any 24 hour period

20 mg-200 mg/10 mL

age | dose
Children under 12 years of age | Do not use
Adults and children over 12 years of age | 10 mL (1 unit dose) every 4 hours

10 mg-100 mg/5 mL

age | dose
Children under 6 years of age | Do not use
Children 6 to under 12 years of age | 5 mL (1 unit dose) every 4 hours
Adults and children over 12 years of age | 10 mL (2 unit dose) every 4 hours

Other Information
• store at 20° to 25°C (68° to 77°F). [See USP Controlled Room Temperature]

• do not use if lid is torn or broken

INACTIVE INGREDIENT

Inactive Ingredients citric acid, FD&C red#40, flavor, menthol, methylparaben, propylene glycol, propylparaben, purified water, sodium citrate, and sucralose.

HOW SUPPLIED

NDC Information -

Each 5 mL of Guaifenesin Syrup and Dextromethorphan contains Guaifenesin 100mg and Dextromethorphan Hydrobromide 10mg and is supplied in the following oral dosage forms:

NDC 57237-312-05 unit dose cup 5mL
NDC 57237-312-51 (100 x 5 mL) unit-dose cups

Each 10 mL of Guaifenesin Syrup and Dextromethorphan contains Guaifenesin 200mg and Dextromethorphan Hydrobromide 20mg and is supplied in the following oral dosage forms:

NDC 57237-313-01 unit dose cup 10mL
NDC 57237-313-18 (80 x 10 mL) unit-dose cups

Questions or comments? Call 1-844-474-7464

Distributed by:

Rising Pharma Holdings, Inc.

East Brunswick, NJ 08816

Issued: 04/2023

PACKAGE LABEL.PRINCIPAL DISPLAY PANEL

10 mg-100 mg/5 mL

Lid Label NDC 57237-312-05

Case Label NDC 57237-312-51

20 mg-200 mg/10 mL

Lid Label NDC 57237-313-01

Case Label NDC 57237-313-18